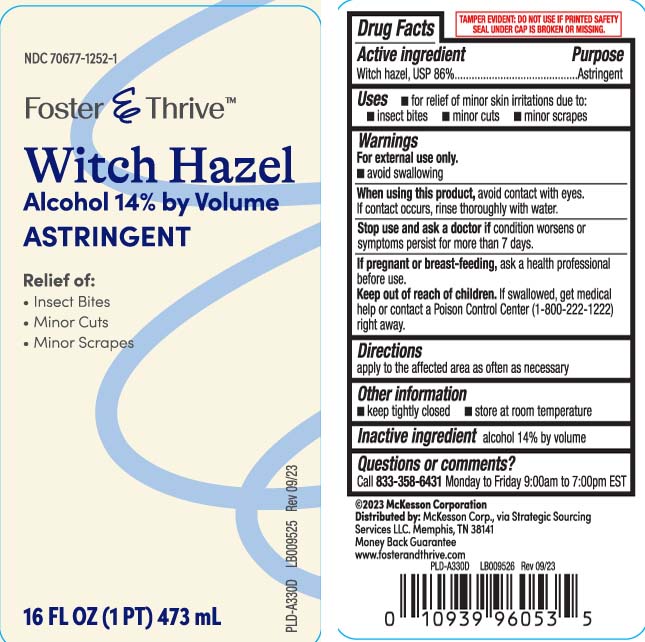 DRUG LABEL: Witch Hazel
NDC: 70677-1252 | Form: LIQUID
Manufacturer: Strategic Sourcing Services LLC
Category: otc | Type: HUMAN OTC DRUG LABEL
Date: 20250414

ACTIVE INGREDIENTS: WITCH HAZEL 842 mg/1 mL
INACTIVE INGREDIENTS: ALCOHOL

Drug Facts

Active ingredient

Witch hazel 86%

Purpose

Astringent

Uses

- for relief of minor skin irritations due to:
  - insect bites
  - minor cuts
  - minor scrapes

Warnings

- for external use only
- avoid swallowing

When using this product

avoid contact with eyes. If contact occurs, rinse thoroughly with water.

Stop use and ask a doctor if

condition worsens or symptoms persist for more than 7 days.

If pregnant or breast-feeding,

ask a health professional before use.

Keep out of reach of children.

If swallowed, get medical help or contact a Poison Control Center (1-800-222-1222) right away.

Directions

apply to the affected area as often as necessary.

Other information

- keep tightly closed
- store at room temperature

Inactive ingredient

alcohol 14% by volume

Principal Display Panel

Witch Hazel

Alcohol 14% by Volume

ASTRINGENT

Relief of:

- Insect Bites
- Minor Cuts
- Minor Scrapes

FL OZ (mL)

TAMPER EVIDENT: DO NOT USE IF PRINTED SAFETY SEAL UNDER CAP IS BROKEN OR MISSING.

Distributed by: McKesson Corp.,

via Strategic Sourcing Services LLC.

Memphis, TN 38141

Package Label

FOSTER & THRIVE Witch Hazel